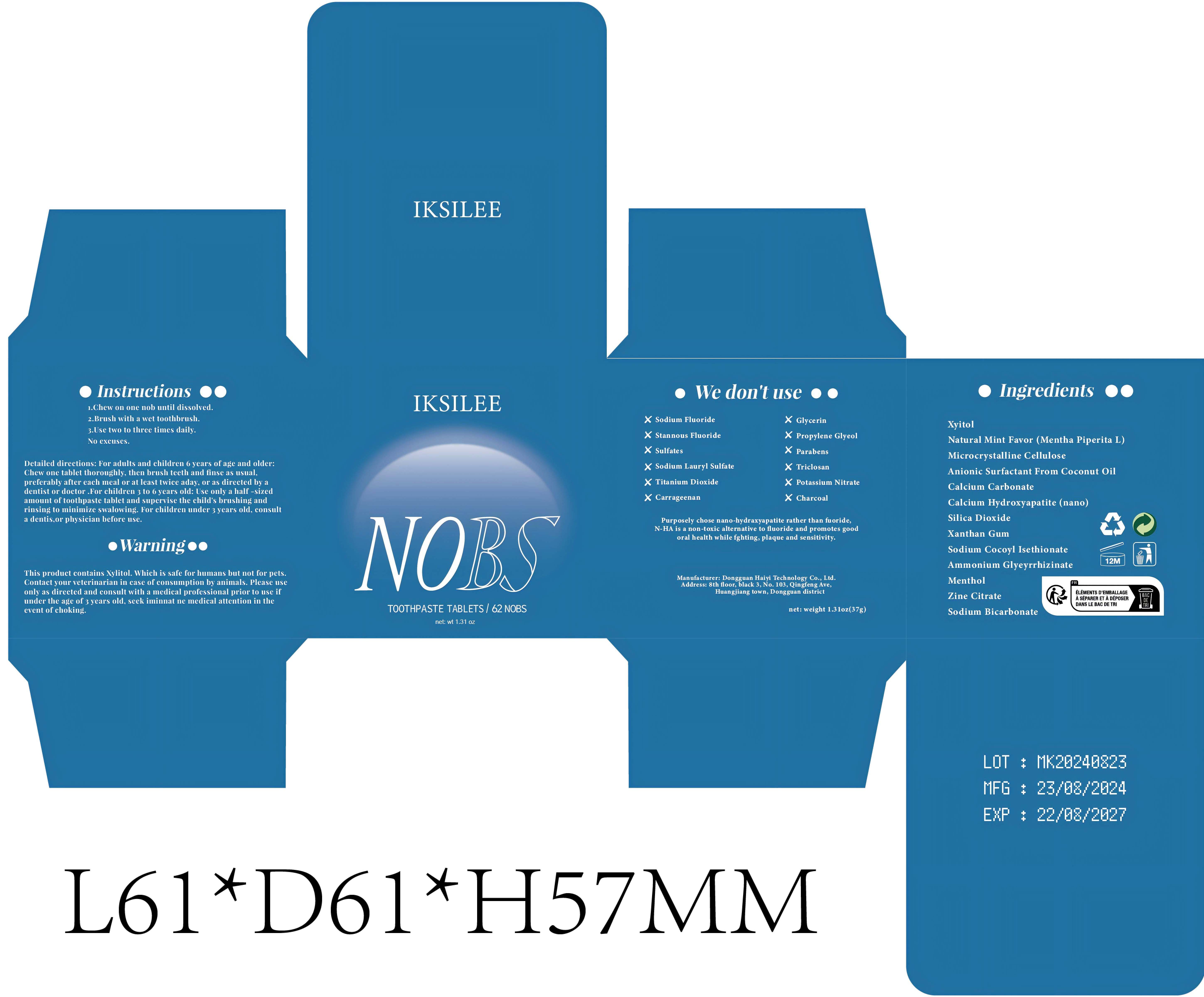 DRUG LABEL: Teeth Cleaning
NDC: 84732-051 | Form: TABLET, CHEWABLE
Manufacturer: Dongguan Haiyi Technology Co.,Ltd.
Category: otc | Type: HUMAN OTC DRUG LABEL
Date: 20241016

ACTIVE INGREDIENTS: XYLITOL 1 mg/100 g; TRIBASIC CALCIUM PHOSPHATE 1 mg/100 g
INACTIVE INGREDIENTS: CALCIUM CARBONATE; XANTHAN GUM; MENTHA PIPERITA LEAF; MICROCRYSTALLINE CELLULOSE; AMMONIUM GLYCYRRHIZATE; COCONUT OIL; SILICON DIOXIDE; SODIUM COCOYL ISETHIONATE; ZINC CITRATE; MENTHOL; SODIUM BICARBONATE

Active ingredient

Xyitol，Natural Mint Favor (Mentha Piperita L)

Inactive ingredient

Microcrystalline Cellulose，Anionic Surfactant From Coconut Oil，Calcium Carbonate，Calcium Hydroxyapatite (nano)，Silica Dioxide，Xanthan Gum，Sodium Cocoyl Isethionate，Ammonium Glyeyrrhizinate，Menthol，Zine Citrate，Sodium Bicarbonate

Purpose section

1.Cleansing teeth: Describing how the product helps in cleaning and removing debris from the teeth.
2.Freshening breath: Indicating the product's ability to reduce bad breath.
3.Whitening teeth: Mentioning any whitening effects, if applicable.
4.Cavity prevention: If fluoride or other ingredients are included, it may state the role in preventing cavities and maintaining oral health.

Warning

This product contains Xylitol. Which is safe for humans but not for pets.Contact your veterinarian in case of consumption by animals. Please useonly as direeted and consult with a medical professional prior to use ifunder the age of 3 years old, seek iminnat ne medical attention in theevent of choking.

stop use

This product may cause allergic reactions in asmall number of people.
lf youexperience any discomfort,please stop using it immediately.

not use

Not suitable for use by children, pregnantor breast feeding people.

OUT OF CHILDREN

KEEP THE PRODUCT OUT OF REACH OF CHILDREN to

HOW TO USE

1.Chew on one nob until dissolved.
2.Brush with a wet toothbrush.
3.Use two to three times daily.
No excuses.

DOSAGE

Once a day in the morning and evening